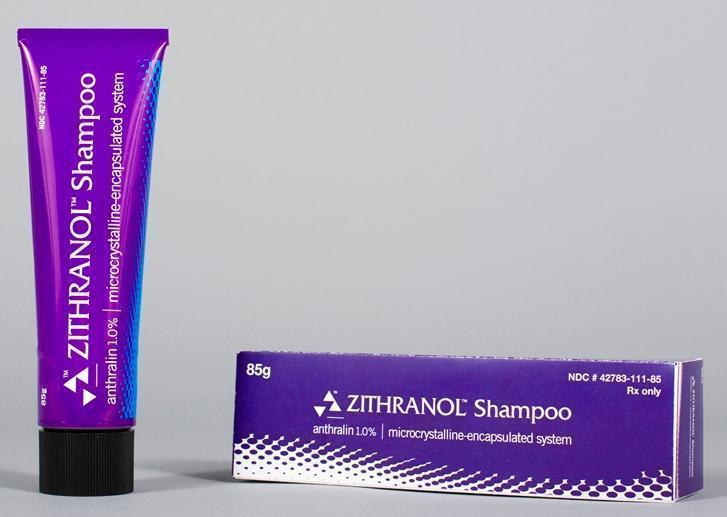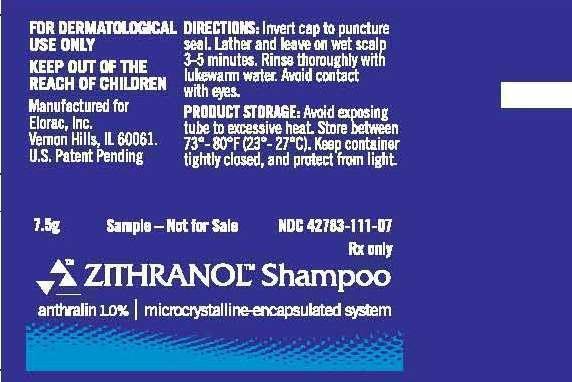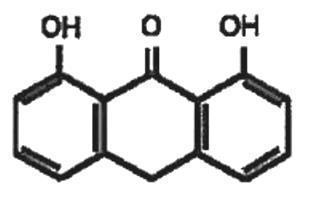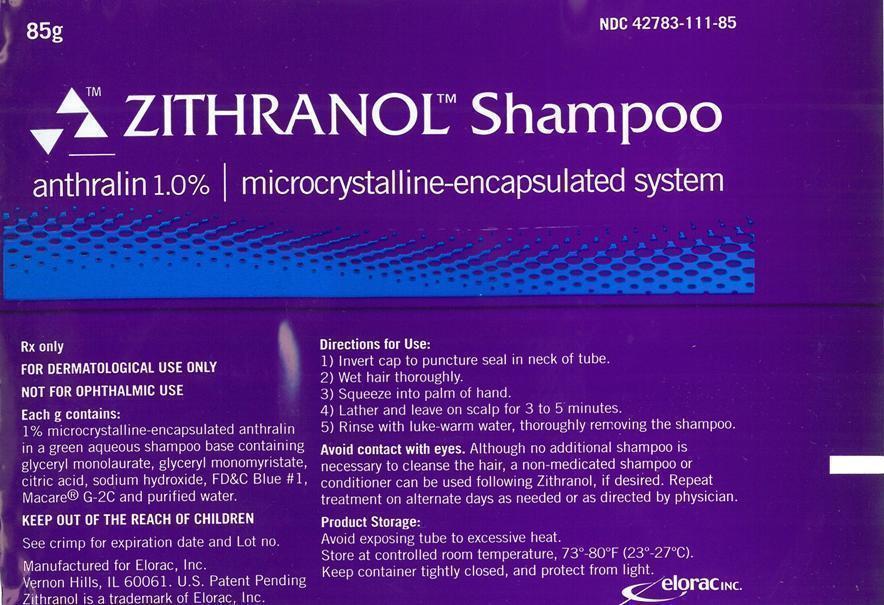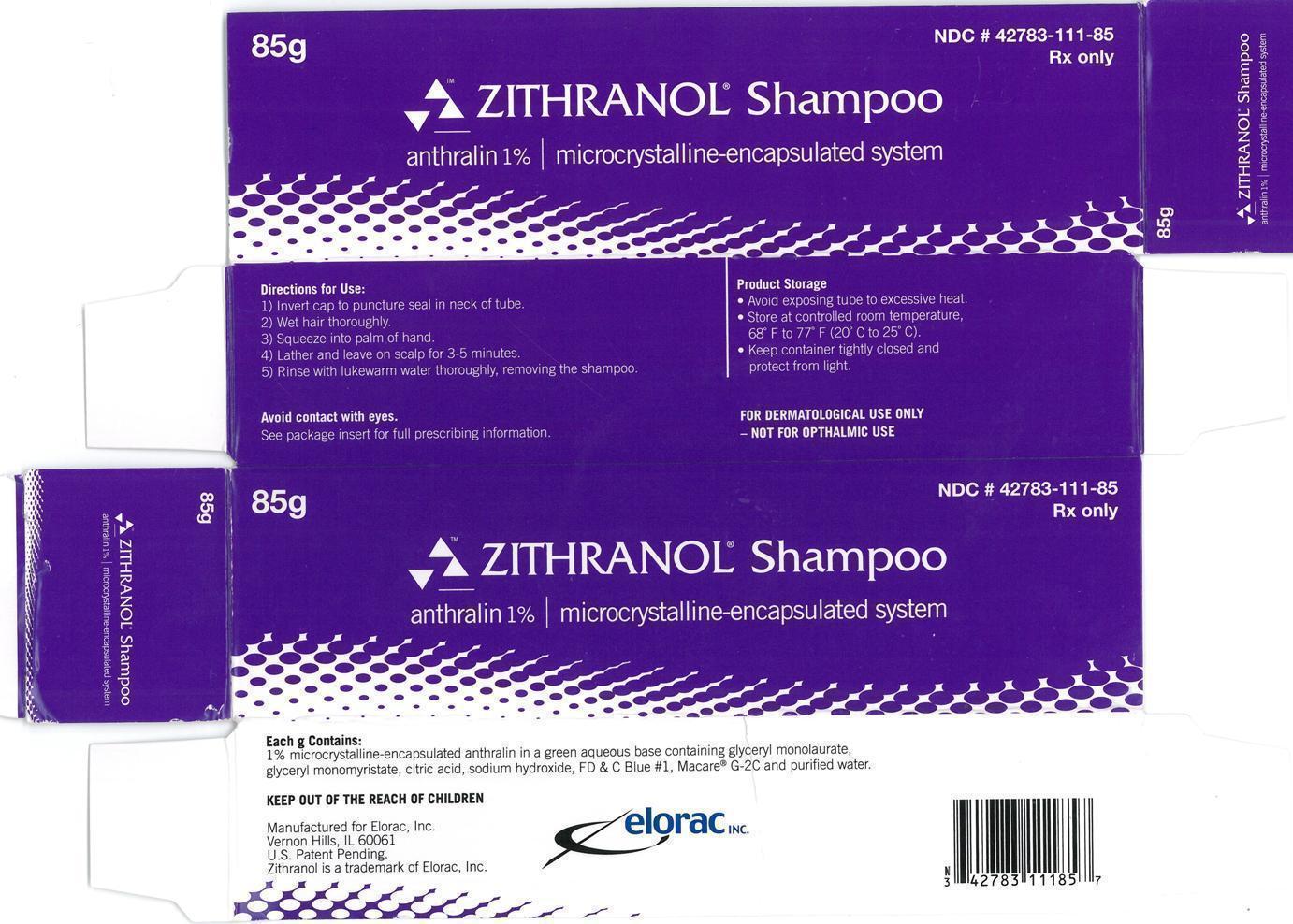 DRUG LABEL: Zithranol
NDC: 42783-111 | Form: SHAMPOO
Manufacturer: Elorac Inc.
Category: prescription | Type: HUMAN PRESCRIPTION DRUG LABEL
Date: 20141017

ACTIVE INGREDIENTS: Anthralin 1 g/100 g
INACTIVE INGREDIENTS: WATER; SODIUM HYDROXIDE; CITRIC ACID MONOHYDRATE; GLYCERYL LAURATE; GLYCERYL MYRISTATE; FD&C BLUE NO. 1; GLYCERETH-2 COCOATE

Zithranol Shampoo anthralin 1% | microcrystalline-encapsulated system Package Insert:

Rx Only

FOR DERMATOLOGIC USE ONLY
NOT FOR OPHTHALMIC USE

DESCRIPTION

Zithranol Shampoo contains 1% anthralin in a shampoo base containing glyceryl monolaurate, glyceryl monomyristate, citric acid, sodium hydroxide, FD&C Blue No. 1, Macare® G-2C, and purified water. The chemical name of anthralin is 1,8-dihydroxy-9-anthrone and its structural formula is:

CLINICAL PHARMACOLOGY

Zithranol Shampoo contains anthralin, a synthetic compound whose precise mechanism of antipsoriatic action is not yet fully understood. However, numerous studies have demonstrated antiproliferative and antiinflammatory effects of anthralin on psoriatic and normal skin. The antiproliferative effects of anthralin appear to result from both an inhibition of DNA synthesis as well as from its strong reducing properties. Recently, anthralin’s effectiveness as an antipsoriatic agent has also been in part attributed to its ability to induce lipid peroxidation and reduce levels of endothelial adhesion molecules, which are markedly elevated in psoriatic patients. Unlike retinoids and PUVA, anthralin does not inhibit liver microsomal enzyme activity; consequently, the likelihood of adverse drug interactions is greatly reduced when other agents are administered concomitantly with anthralin.

INDICATIONS AND USAGE

Zithranol Shampoo for the treatment of scalp psoriasis in subjects 12 years of age and older (see PRECAUTIONS). Patients should be instructed to use Zithranol Shampoo for the minimum time period necessary to achieve the desired results.

CONTRAINDICATIONS

Use of Zithranol Shampoo is contraindicated in patients who are hypersensitive to anthralin or to any ingredient in this preparation.

WARNINGS

Avoid contact with the eyes or mucous membranes. Discontinue use if a sensitivity reaction occurs or if excessive irritation develops.

PRECAUTIONS

General: For external use only. Contact with fabrics, plastics and other materials may cause staining and should be avoided. Always wash hands thoroughly after use. Keep container tightly capped when not in use. Avoid excessive heat. Keep out of the reach of children.

Carcinogenesis, mutagenesis, impairment of fertility: Although long-term studies in animals have not been performed to evaluate the carcinogenic potential of the drug, there have been no reports to suggest carcinogenic effects in humans after many years of clinical use.

Pregnancy:
Teratogenic Effects: Pregnancy Category C
Animal reproduction studies have not been conducted with Zithranol Shampoo. It is also not known whether Zithranol Shampoo can cause fetal harm when administered to a pregnant woman or can affect reproduction capacity. Zithranol Shampoo should be given to a pregnant woman only if clearly needed.

Nursing mothers: Because many drugs are excreted in human milk, caution should be exercised when Zithranol Shampoo is administered to a nursing woman.

Pediatric use: Safety and effectiveness in children have not been established.

ADVERSE REACTIONS

Very few instances of contact allergic reactions to anthralin have been reported. Transient primary irritation and staining of hair or skin may occur. The temporary discoloration of hair and skin may be minimized by careful application. Staining of fabrics may be permanent so contact should be avoided.

DOSAGE AND ADMINISTRATION

Zithranol Shampoo should be applied onto wet scalp 3 to 4 times per week (or as directed by the physician). Lather and leave on scalp for 3 to 5 minutes and then rinse thoroughly. Avoid contact with eyes. Although no additional shampoo is necessary to cleanse the hair, a non-medicated shampoo or conditioner can be applied following the use of Zithranol Shampoo, if desired. If no improvement is seen after 4 weeks of treatment, consult the physician.

HOW SUPPLIED

Zithranol Shampoo (anthralin 1%) microcrystalline-encapsulated system is supplied in tubes.

85g NDC 42783-111-85
7.5g NDC 42783-111-07
(physician sample size)

Store at controlled room temperature 68°F to 77°F (20°C to 25°C).

Manufactured for:
Elorac, Inc.
Vernon Hills, IL 60061

U.S. Patent Pending

Caution: Federal law prohibits dispensing without prescription.

© 2011 Elorac, Inc.

Rev. 01 (10/2011)

TUBE AND CARTON PHOTO:

Zithranol Shampoo anthralin 1% | microcrystalline encapsulated system 85g Carton Label:

NDC 42783-111-85

Zithranol Shampoo
anthralin 1% | microcrystalline-encapsulated system
85g

FOR DERMATOLOGIC USE ONLY
NOT FOR OPHTHALMIC USE

Rx only

Zithranol Shampoo anthralin 1% | microcrystalline encapsulated system 85g Container Label:

NDC 42783-111-85

Zithranol Shampoo
anthralin 1% | microcrystalline-encapsulated system
85g

FOR DERMATOLOGIC USE ONLY
NOT FOR OPHTHALMIC USE

Rx only

Zithranol Shampoo anthralin 1% | microcrystalline-encapsulated system 7.5g Physician Sample Container Label:

NDC 42783-111-07

Zithranol Shampoo
anthralin 1% | microcrystalline-encapsulated system
7.5g

FOR DERMATOLOGIC USE ONLY
NOT FOR OPHTHALMIC USE

Rx only